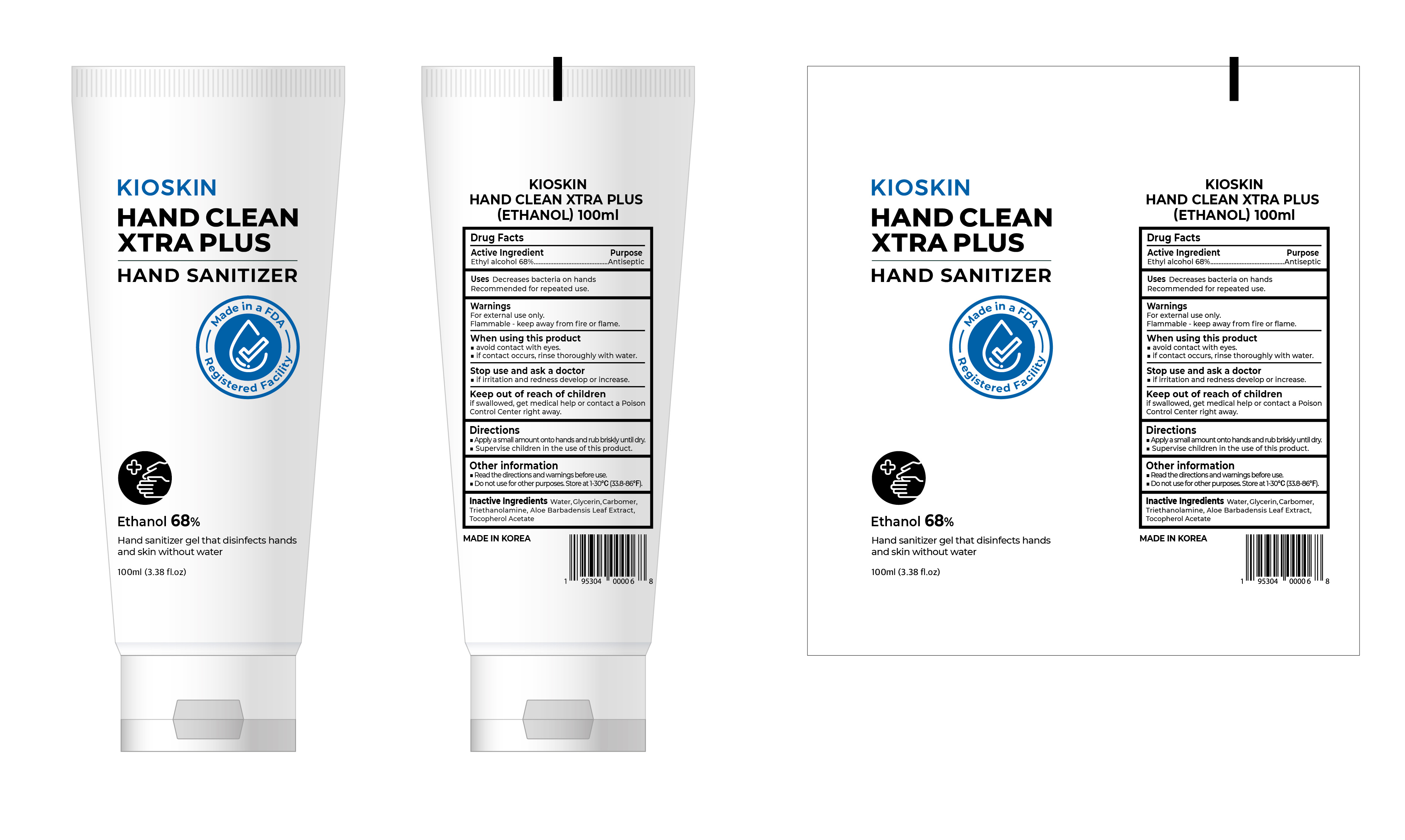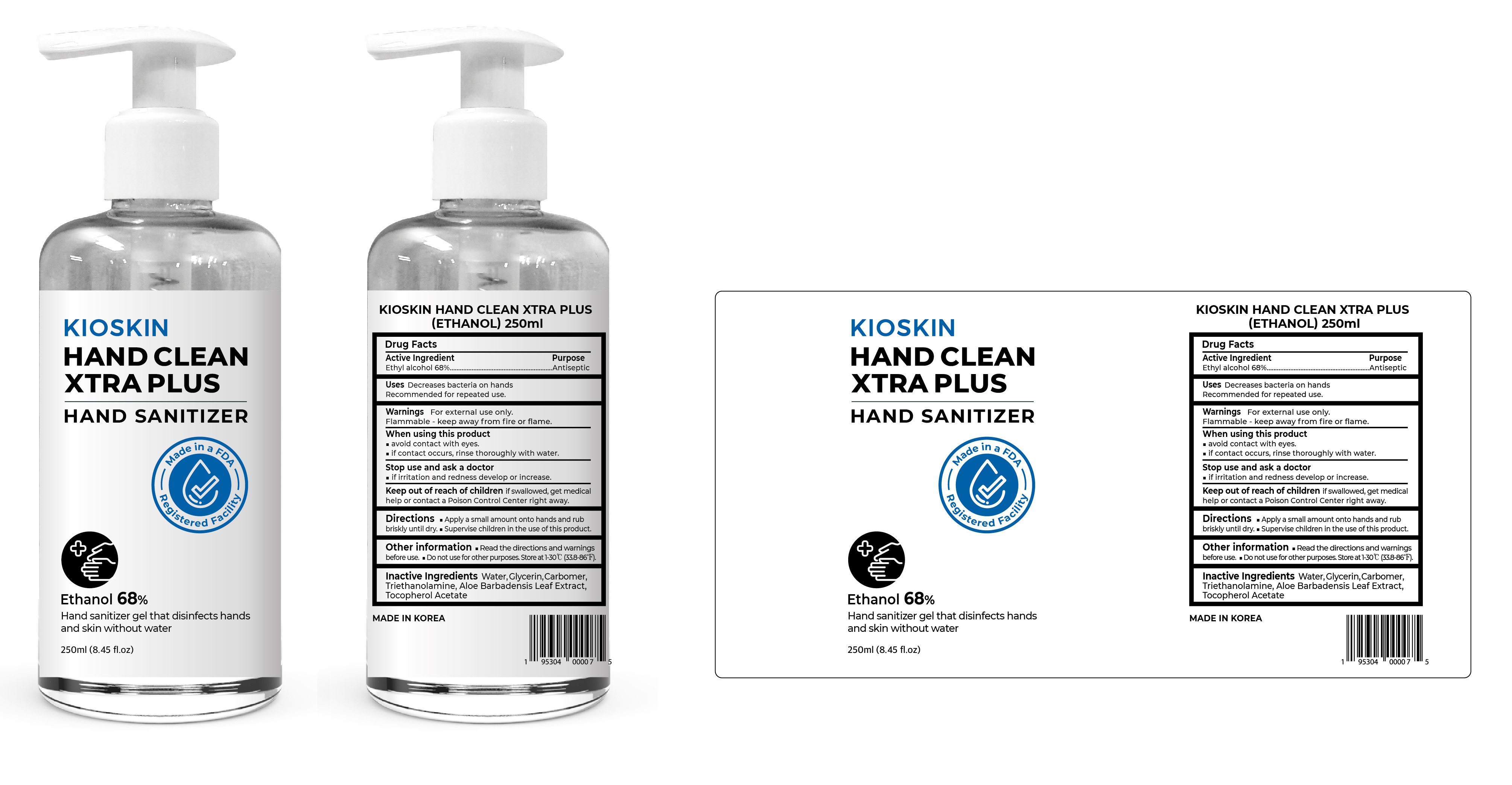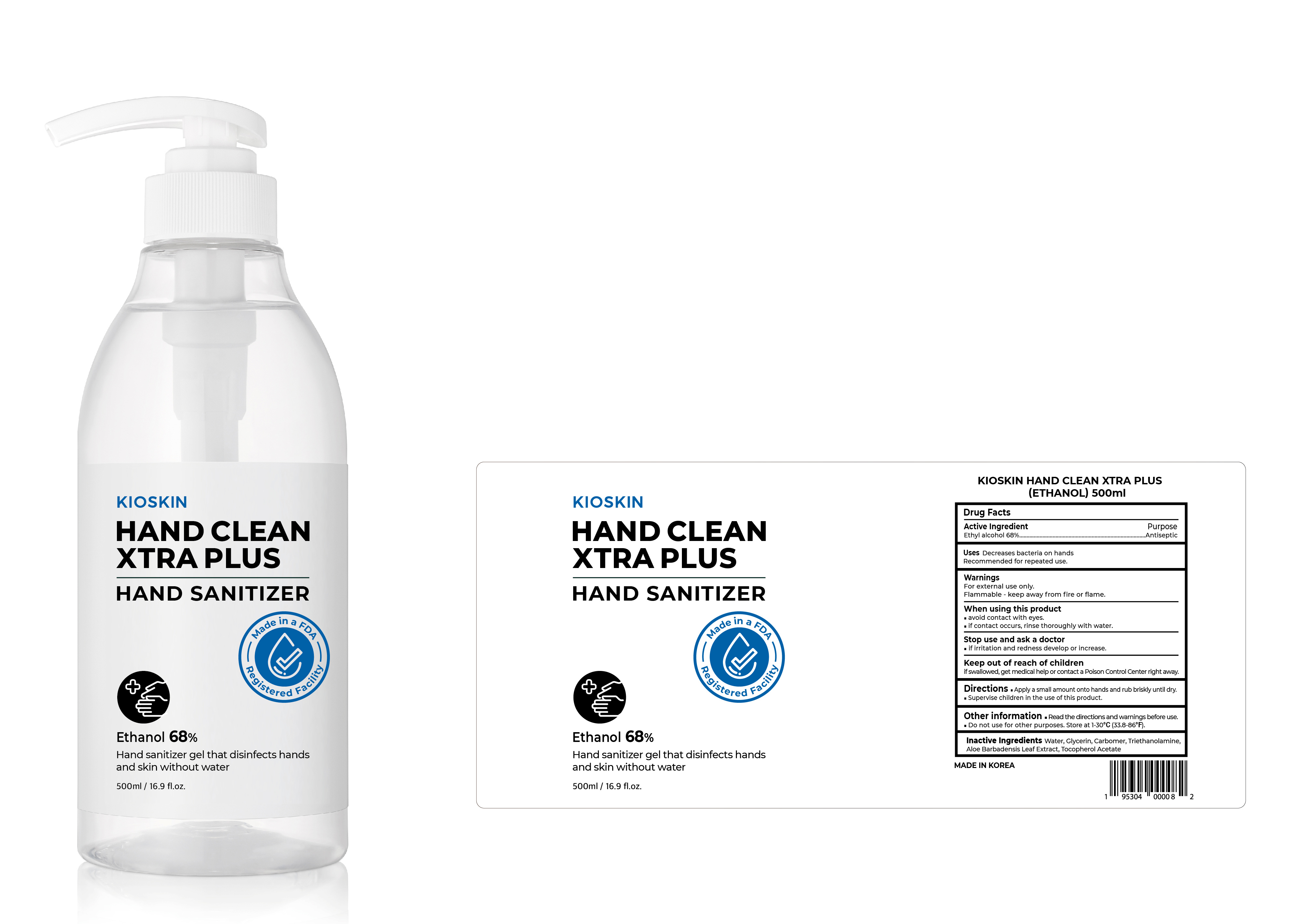 DRUG LABEL: KIOSKIN HAND CLEAN XTRA PLUS (ETHANOL)
NDC: 73330-0017 | Form: GEL
Manufacturer: COSNINE, Inc.
Category: otc | Type: HUMAN OTC DRUG LABEL
Date: 20200625

ACTIVE INGREDIENTS: ALCOHOL 0.68 mL/1 mL
INACTIVE INGREDIENTS: .ALPHA.-TOCOPHEROL ACETATE, D-; ALOE VERA LEAF; GLYCERIN; CARBOMER HOMOPOLYMER TYPE C (ALLYL PENTAERYTHRITOL CROSSLINKED); WATER; TROLAMINE

Active Ingredient(s)

Ethyl Alcohol 68%

Purpose

Antiseptic

Uses

Decrease bacteria on hands
Recommended for repeated use.

Warnings

For external use only.

Flammable - Keep away from fire or flame

When using this product

avoid contact with eyes.

if contact occurs, rinse thoroughly with waterr

Stop use and ask a doctor

if irritation and redness develop or increase.

Keep out of reach of children

if swallowed, get medical help or contact a Poison Control Center right away.

Directions

- Apply a small amount onto hands and rub briskly until dry.
- Supervise children in the use of this product.

Other information

- Read the directions and warnings before use.
- Do not use for other purposes.
- Store at 1-30℃ (33.8-86℉).

Inactive ingredients

Water, Glycerin, Carbomer, Triethanolamine, Aloe Barbadensis Leaf Extract, Tocopherol Acetate

Package Label - Principal Display Panel

500 mL NDC: 73330-0017-1

250 mL NDC: 73330-0017-2

100 mL NDC: 73330-0017-3